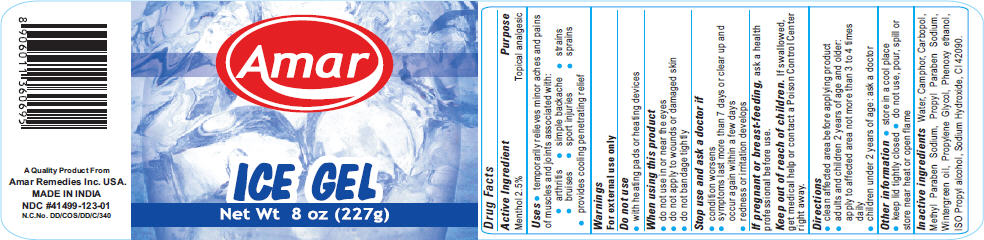 DRUG LABEL: Amar Ice
NDC: 41499-123 | Form: GEL
Manufacturer: AMAR REMEDIES LIMITED
Category: otc | Type: HUMAN OTC DRUG LABEL
Date: 20110414

ACTIVE INGREDIENTS: Menthol 2.5 g/100 g
INACTIVE INGREDIENTS: Camphor (Synthetic) 0.7 g/100 g; MethylParaben Sodium; PropylParaben Sodium; Methyl Salicylate; Propylene Glycol; Phenoxyethanol; Propyl Alcohol; Water

Amar
ICE GEL

Drug Facts

Active Ingredient

Menthol 2.5%

Purpose

Topical analgesic

Uses

- temporarily relieves minor aches and pains of muscles and joints associated with:
  - arthritis
  - bruises
  - simple backache
  - sport injuries
  - strains
  - sprains
- provides cooling penetrating relief

Warnings

For external use only

Do not use

- with heating pads or heating devices

When using this product

- do not use in or near the eyes
- do not apply to wounds or damaged skin
- do not bandage tightly

Stop use and ask a doctor if

- condition worsens
- symptoms last more than 7 days or clear up and occur again within a few days
- redness or irritation develops

PREGNANCY OR BREAST FEEDING

If pregnant or breast-feeding, ask a health professional before use.

Keep out of reach of children. If swallowed, get medical help or contact a Poison Control Center right away.

Directions

- clean affected area before applying product
- adults and children 2 years of age and older: apply to affected area not more than 3 to 4 times daily
- children under 2 years of age: ask a doctor

Other information

- store in a cool place
- keep lid tightly closed
- do not use, pour, spill or store near heat or open flame

Inactive ingredients

Water, Camphor, Carbopol, Methyl Paraben Sodium, Propyl Paraben Sodium, Wintergreen oil, Propylene Glycol, Phenoxy ethanol, ISO Propyl alcohol, Sodium Hydroxide, Cl 42090.

PRINCIPAL DISPLAY PANEL - 227 g Jar Label

Amar

ICE GEL

Net Wt 8 oz (227g)